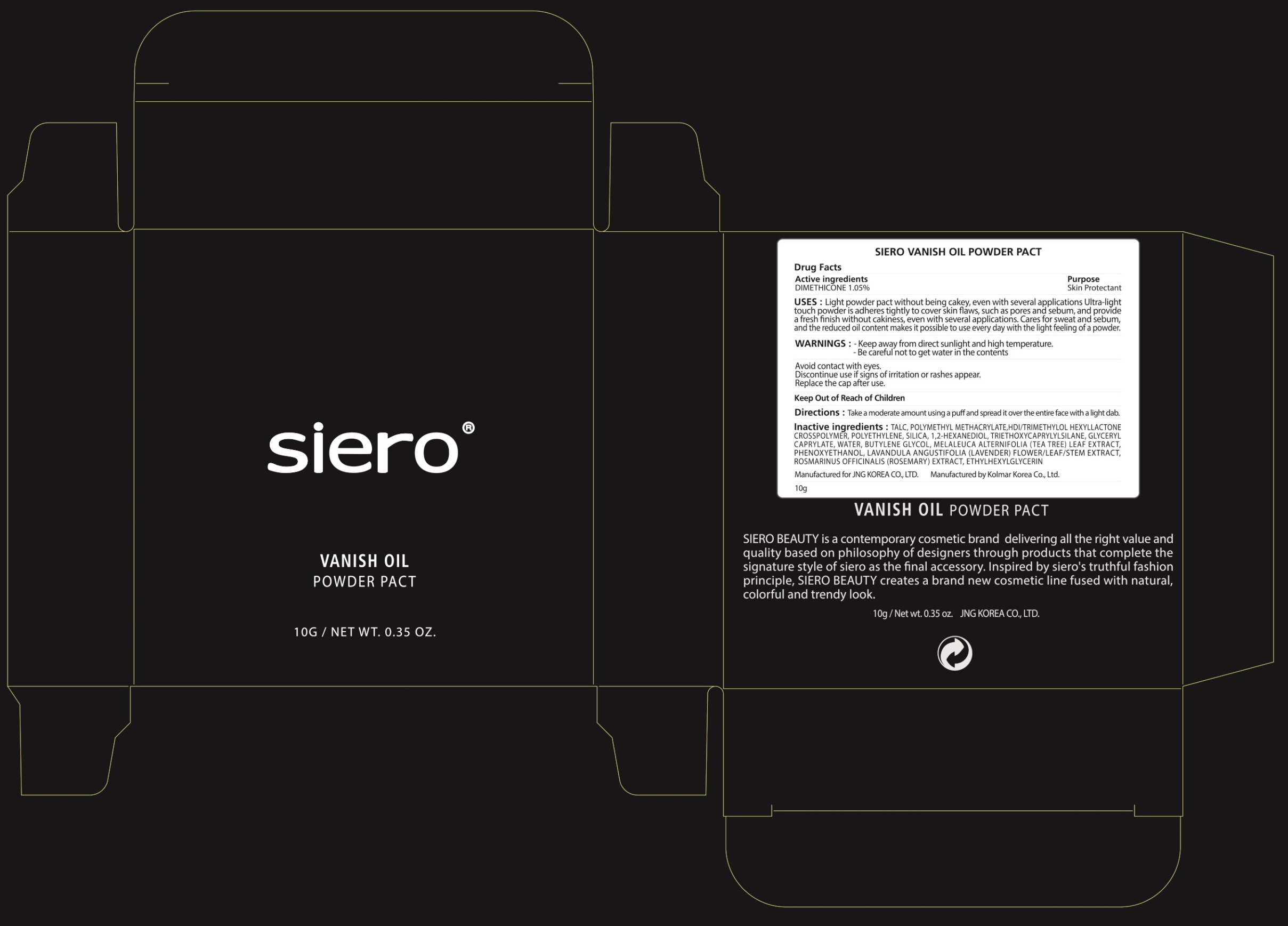 DRUG LABEL: SIERO VANISH OI L POWDE R PACT
NDC: 71472-260 | Form: POWDER
Manufacturer: JNG KOREA CO.,LTD.
Category: otc | Type: HUMAN OTC DRUG LABEL
Date: 20170630

ACTIVE INGREDIENTS: DIMETHICONE 1.05 g/10 g
INACTIVE INGREDIENTS: TALC; 1,2-HEXANEDIOL

ACTIVE INGREDIENT

Active ingredients: DIMETHICONE 1.05%

INACTIVE INGREDIENT

Inactive ingredients: TALC, POLYMETHYL METHACRYLATE,HDI/TRIMETHYLOL HEXYLLACTONE CROSSPOLYMER, POLYETHYLENE, SILICA, 1,2-HEXANEDIOL, TRIETHOXYCAPRYLYLSILANE, GLYCERYL CAPRYLATE, WATER, BUTYLENE GLYCOL, MELALEUCA ALTERNIFOLIA (TEA TREE) LEAF EXTRACT, PHENOXYETHANOL, LAVANDULA ANGUSTIFOLIA (LAVENDER) FLOWER/LEAF/STEM EXTRACT, ROSMARINUS OFFICINALIS (ROSEMARY) EXTRACT, ETHYLHEXYLGLYCERIN

PURPOSE

Purpose: Skin Protectant

WARNINGS

Warnings: - Keep away from direct sunlight and high temperature. - For external use only Avoid contact with eyes. Discontinue use if signs of irritation or rashes appear. Replace the cap after use.

KEEP OUT OF REACH OF CHILDREN

Uses

Uses: Light powder pact without being cakey, even with several applications Ultra-light touch powder is adheres tightly to cover skin flaws, such as pores and sebum, and provide a fresh finish without cakiness, even with several applications. Cares for sweat and sebum, and the reduced oil content makes it possible to use every day with the light feeling of a powder.

Directions

Directions: Take a moderate amount using a puff and spread it over the entire face with a light dab.